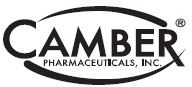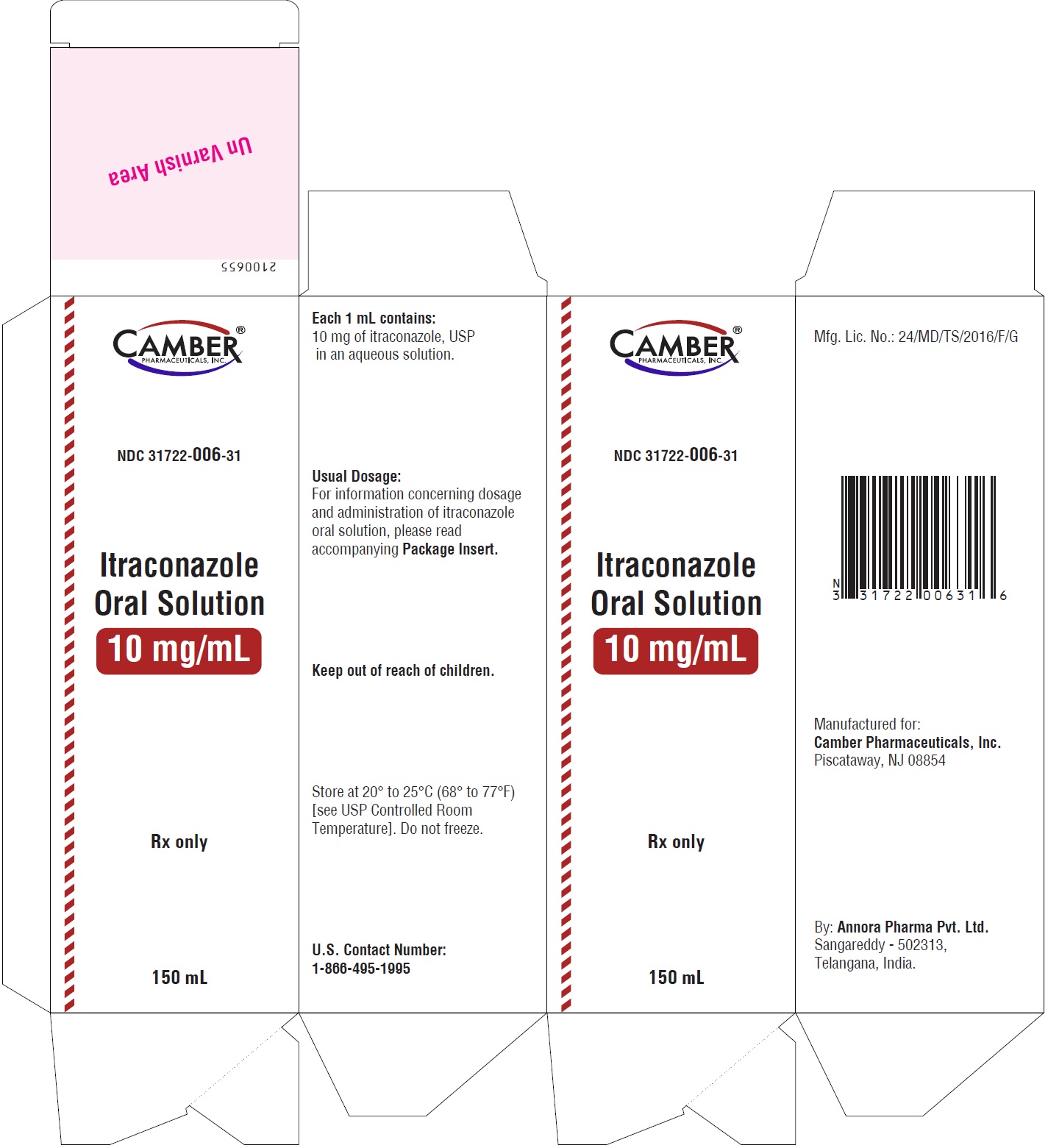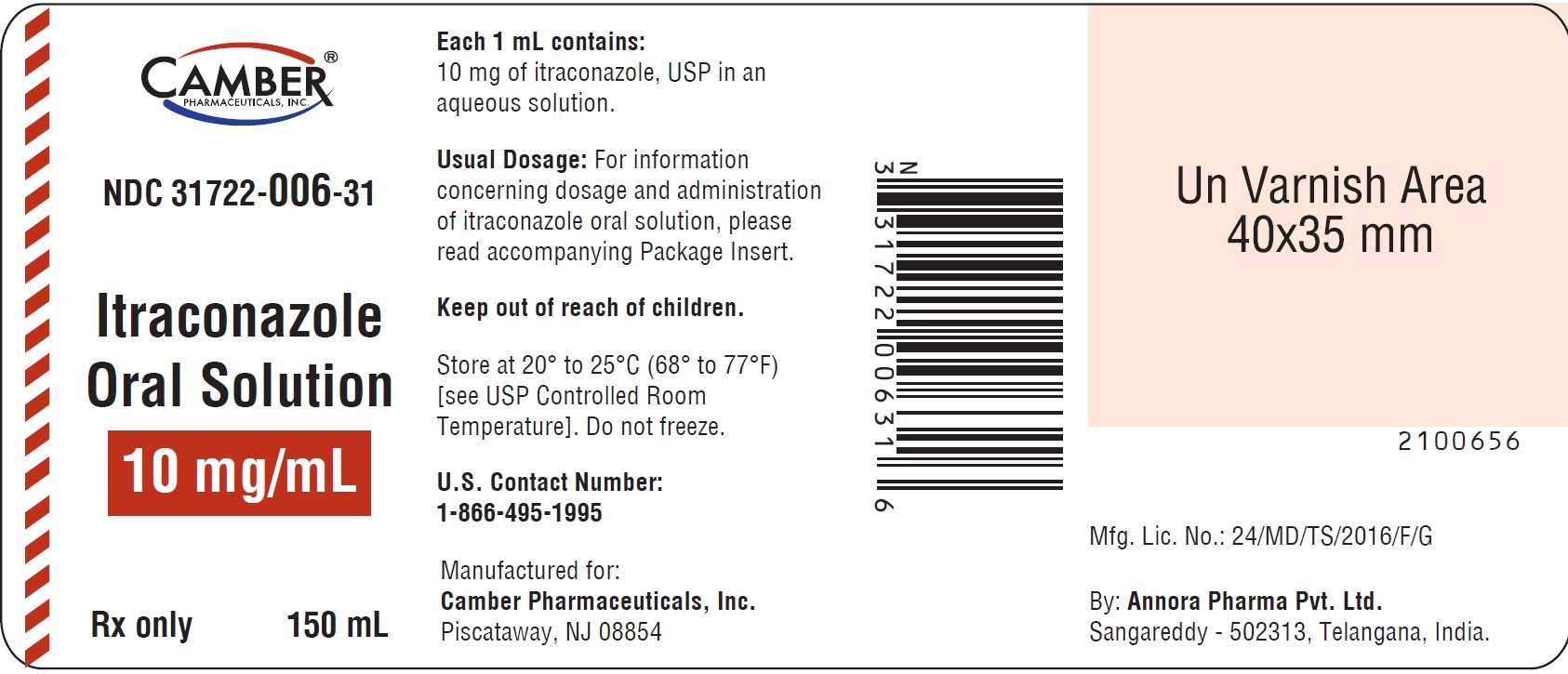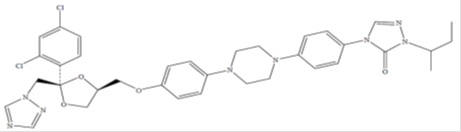 DRUG LABEL: Itraconazole

NDC: 31722-006 | Form: SOLUTION
Manufacturer: Camber Pharmaceuticals, Inc.
Category: prescription | Type: HUMAN PRESCRIPTION DRUG LABEL
Date: 20250129

ACTIVE INGREDIENTS: ITRACONAZOLE 10 mg/1 mL
INACTIVE INGREDIENTS: ASCORBIC ACID; HYDROCHLORIC ACID; PROPYLENE GLYCOL; WATER; NONCRYSTALLIZING SORBITOL SOLUTION; SACCHARIN SODIUM; SODIUM HYDROXIDE

Itraconazole Oral Solution

BOXED WARNING

Congestive Heart Failure, Cardiac Effects and Drug Interactions
Congestive Heart Failure and Cardiac Effects:
• If signs or symptoms of congestive heart failure occur during administration of itraconazole oral solution, continued itraconazole oral
solution use should be reassessed.
• When itraconazole was administered intravenously to dogs and healthy human volunteers, negative inotropic effects were seen. (See CONTRAINDICATIONS, WARNINGS, PRECAUTIONS: Drug Interactions, ADVERSE REACTIONS: Postmarketing Experience, and CLINICAL PHARMACOLOGY: Special Populations for more information.)
Drug Interactions:
• Coadministration of a number of CYP3A4 substrates are contraindicated with itraconazole oral solution. Some examples of drugs that are contraindicated for coadministration with itraconazole oral solution are: methadone, disopyramide, dofetilide, dronedarone, quinidine, isavuconazole, ergot alkaloids (such as dihydroergotamine, ergometrine (ergonovine), ergotamine, methylergometrine (methylergonovine)), irinotecan, lurasidone, oral midazolam, pimozide, triazolam, felodipine, nisoldipine, ivabradine, ranolazine, eplerenone, cisapride, naloxegol, lomitapide, lovastatin, simvastatin, avanafil, ticagrelor, finerenone, voclosporin.
• Coadministration with colchicine, fesoterodine and solifenacin is contraindicated in subjects with varying degrees of renal or hepatic impairment.
• Coadministration with eliglustat is contraindicated in subjects that are poor or intermediate metabolizers of CYP2D6 and in subjects taking strong or moderate CYP2D6 inhibitors.
• Coadministration with venetoclax is contraindicated in patients with chronic lymphocytic leukemia (CLL)/small lymphocytic lymphoma (SLL) during the dose initiation and ramp-up phase of venetoclax. See PRECAUTIONS: Drug Interactions Section for specific examples.
• Coadministration with itraconazole can cause elevated plasma concentrations of these drugs and may increase or prolong both the pharmacologic effects and/or adverse reactions to these drugs. For example, increased plasma concentrations of some of these drugs can lead to QT prolongation and ventricular tachyarrhythmias including occurrences of torsade de pointes, a potentially fatal arrhythmia. See CONTRAINDICATIONS and WARNINGS Sections, and PRECAUTIONS: Drug Interactions Section for specific examples.

DESCRIPTION

Itraconazole, an azole antifungal agent. Itraconazole is a 1:1:1:1 racemic mixture of four diastereomers (two enantiomeric pairs), each possessing three chiral centers. It may be represented by the following structural formula and nomenclature:

(±)-1-sec-Butyl-4-[p-[4-[p-[[2R*,4S*)-2-(2,4-dichloro phenyl)-2-(1H-1, 2, 4-triazol-1 ylmethyl)-1,3- dioxolan-4 yl]methoxy]phenyl]-1-piperazinyl]phenyl]- Δ^2-1, 2, 4-triazolin-5- one
or
4-[4-[4-[4-[[Cis-2-(2,4-dichlorophenyl)-2-(1H-1,2,4- triazol-1-ylmethyl)-1,3-dioxolan-4 yl]methoxy] phenyl]piperazin-1-yl] phenyl]-2-[(1RS)-1-methyl propyl]-2,4-dihydro-3H-1,2,4-triazol-3-one
Itraconazole has a molecular formula of C35H38Cl2N8O4and a molecular weight of 705.63. It is a white or almost white powder. It is freely soluble in methylene chloride, sparingly soluble in tetrahydrofuran, very slightly soluble in alcohol, practically insoluble in water. It has a pKa of 3.70 (based on extrapolation of values obtained from methanolic solutions) and a log (n-octanol/ aq. Buffer of pH: 8.1) partition coefficient of 5.66 at pH 8.1.
Itraconazole oral solution contains 10 mg of itraconazole USP per mL, solubilized by hydroxypropyl-β-cyclodextrin (400 mg/mL) as a molecular inclusion complex. Itraconazole oral solution is clear, colorless to yellowish brown liquid with a target pH of 2. Other ingredients are ascorbic acid, hydrochloric acid, propylene glycol, purified water, non crystallizing sorbitol solution, saccharin sodium, sodium hydroxide, ART Cherry flavor.

CLINICAL PHARMACOLOGY

Pharmacokinetics and Metabolism:

Itraconazole

General Pharmacokinetic Characteristics

Peak plasma concentrations are reached within 2.5 hours following administration of the oral solution. As a consequence of non-linear pharmacokinetics, itraconazole accumulates in plasma during multiple dosing. Steady-state concentrations are generally reached within about 15 days, with Cmaxand AUC values 4 to 7-fold higher than those seen after a single dose. Steady-state Cmaxvalues of about 2 mcg/mL are reached after oral administration of 200 mg once daily. The terminal half-life of itraconazole generally ranges from 16 to 28 hours after single dose and increases to 34 to 42 hours with repeated dosing. Once treatment is stopped, itraconazole plasma concentrations decrease to an almost undetectable concentration within 7 to 14 days, depending on the dose and duration of treatment. Itraconazole mean total plasma clearance following intravenous administration is 278 mL/min. Itraconazole clearance decreases at higher doses due to saturable hepatic metabolism.

Absorption

Itraconazole is rapidly absorbed after administration of the oral solution. Peak plasma concentrations of itraconazole are reached within 2.5 hours following administration of the oral solution under fasting conditions. The observed absolute bioavailability of itraconazole under fed conditions is about 55% and increases by 30% when the oral solution is taken in fasting conditions. Itraconazole exposure is greater with the oral solution than with the capsule formulation when the same dose of drug is given. (see WARNINGS)

Distribution

Most of the itraconazole in plasma is bound to protein (99.8%), with albumin being the main binding component (99.6% for the hydroxy-metabolite). It has also a marked affinity for lipids. Only 0.2% of the itraconazole in plasma is present as free drug. Itraconazole is distributed in a large apparent volume in the body (>700 L), suggesting extensive distribution into tissues. Concentrations in lung, kidney, liver, bone, stomach, spleen and muscle were found to be two to three times higher than corresponding concentrations in plasma, and the uptake into keratinous tissues, skin in particular, up to four times higher. Concentrations in the cerebrospinal fluid are much lower than in plasma.

Metabolism

Itraconazole is extensively metabolized by the liver into a large number of metabolites. In vitrostudies have shown that CYP3A4 is the major enzyme involved in the metabolism of itraconazole. The main metabolite is hydroxy-itraconazole, which has in vitroantifungal activity comparable to itraconazole; trough plasma concentrations of this metabolite are about twice those of itraconazole.

Excretion
Itraconazole is excreted mainly as inactive metabolites in urine (35%) and in feces (54%) within one week of an oral solution dose. Renal excretion of itraconazole and the active metabolite hydroxy-itraconazole account for less than 1% of an intravenous dose. Based on an oral radiolabeled dose, fecal excretion of unchanged drug ranges from 3% to 18% of the dose.

Special Populations:
Renal Impairment:
Limited data are available on the use of oral itraconazole in patients with renal impairment. A pharmacokinetic study using a single 200 mg oral dose of itraconazole was conducted in three groups of patients with renal impairment (uremia: n = 7; hemodialysis: n = 7; and continuous ambulatory peritoneal dialysis: n = 5). In uremic subjects with a mean creatinine clearance of 13 mL/min.×1.73 m^2, the exposure, based on AUC, was slightly reduced compared with normal population parameters. This study did not demonstrate any significant effect of hemodialysis or continuous ambulatory peritoneal dialysis on the pharmacokinetics of itraconazole (Tmax, Cmax, and AUC0 to 8h). Plasma concentration-versus-time profiles showed wide intersubject variation in all three groups.

After a single intravenous dose, the mean terminal half-lives of itraconazole in patients with mild (defined in this study as CrCl 50 to 79 mL/min), moderate (defined in this study as CrCl 20 to 49 mL/min), and severe renal impairment (defined in this study as CrCl <20 mL/min) were similar to that in healthy subjects (range of means 42 to 49 hours vs 48 hours in renally impaired patients and healthy subjects, respectively). Overall exposure to itraconazole, based on AUC, was decreased in patients with moderate and severe renal impairment by approximately 30% and 40%, respectively, as compared with subjects with normal renal function.

Data are not available in renally impaired patients during long-term use of itraconazole. Dialysis has no effect on the half-life or clearance of itraconazole or hydroxy-itraconazole. (See PRECAUTIONS and DOSAGE AND ADMINISTRATION.)

Hepatic Impairment:

Itraconazole is predominantly metabolized in the liver. A pharmacokinetic study was conducted in 6 healthy and 12 cirrhotic subjects who were administered a single 100 mg dose of itraconazole as capsule. A statistically significant reduction in mean Cmax(47%) and a two fold increase in the elimination half-life (37 ± 17 hours vs. 16 ± 5 hours) of itraconazole were noted in cirrhotic subjects compared with healthy subjects. However, overall exposure to itraconazole, based on AUC, was similar in cirrhotic patients and in healthy subjects. Data are not available in cirrhotic patients during long-term use of itraconazole. (See CONTRAINDICATIONS, PRECAUTIONS: Drug Interactions and DOSAGE AND ADMINISTRATION.)

Decreased Cardiac Contractility:
When itraconazole was administered intravenously to anesthetized dogs, a dose-related negative inotropic effect was documented. In a healthy volunteer study of itraconazole intravenous infusion, transient, asymptomatic decreases in left ventricular ejection fraction were observed using gated SPECT imaging; these resolved before the next infusion, 12 hours later. If signs or symptoms of congestive heart failure appear during administration of itraconazole oral solution, monitor carefully and consider other treatment alternatives which may include discontinuation of itraconazole oral solution administration. (See BOXED WARNING, CONTRAINDICATIONS, WARNINGS, PRECAUTIONS: Drug Interactions and ADVERSE REACTIONS: Postmarketing Experience for more information.)

Cystic Fibrosis:
Seventeen cystic fibrosis patients, ages 7 to 28 years old, were administered itraconazole oral solution 2.5 mg/kg b.i.d. for 14 days in a pharmacokinetic study. Sixteen patients completed the study. Steady state trough concentrations >250 ng/mL were achieved in 6 out of 11 patients ≥16 years of age but in none of the 5 patients <16 years of age. Large variability was observed in the pharmacokinetic data (%CV for trough concentrations = 98% and 70% for ≥16 and <16 years, respectively; %CV for AUC = 75% and 58% for ≥16 and <16 years, respectively). If a patient with cystic fibrosis does not respond to itraconazole oral solution, consideration should be given to switching to alternative therapy.

Hydroxypropyl-ß-Cyclodextrin:
The oral bioavailability of hydroxypropyl-β-cyclodextrin given as a solubilizer of itraconazole in oral solution is on average lower than 0.5% and is similar to that of hydroxypropyl-β-cyclodextrin alone. This low oral bioavailability of hydroxypropyl-β-cyclodextrin is not modified by the presence of food and is similar after single and repeated administrations.

MICROBIOLOGY

Mechanism of Action:
In vitrostudies have demonstrated that itraconazole inhibits the cytochrome P450-dependent synthesis of ergosterol, which is a vital component of fungal cell membranes.
Antimicrobial Activity:
Itraconazole has been shown to be active against most strains of the following microorganism,

both in vitroand in clinical infections.
Candida albicans
Susceptibility Testing Methods:
For specific information regarding susceptibility test interpretive criteria and associated test methods and quality control standards recognized by FDA for this drug, please see: https://www.fda.gov/STIC.
Drug Resistance:
Isolates from several fungal species with decreased susceptibility to itraconazole have been isolated in vitroand from patients receiving prolonged therapy.
Candida krusei, Candida glabrataand Candida tropicalisare generally the least susceptible Candidaspecies, with some isolates showing unequivocal resistance to itraconazole in vitro.
Itraconazole is not active against Zygomycetes(e.g., Rhizopusspp., Rhizomucorspp., Mucorspp. and Absidiaspp.), Fusariumspp., Scedosporiumspp. and Scopulariopsisspp.
Cross-Resistance:
In systemic candidosis, if fluconazole-resistant strains of Candidaspecies are suspected, it cannot be assumed that these are sensitive to itraconazole, hence their sensitivity should be tested before the start of itraconazole therapy.
Several in vitrostudies have reported that some fungal clinical isolates, including Candidaspecies, with reduced susceptibility to one azole antifungal agent may also be less susceptible to other azole derivatives. The finding of cross-resistance is dependent on a number of factors, including the species evaluated, its clinical history, the particular azole compounds compared, and the type of susceptibility test that is performed.
Studies (both in vitroand in vivo) suggest that the activity of amphotericin B may be suppressed by prior azole antifungal therapy. As with other azoles, itraconazole inhibits the^14C-demethylation step in the synthesis of ergosterol, a cell wall component of fungi. Ergosterol is the active site for amphotericin B. In one study the antifungal activity of amphotericin B against Aspergillus fumigatusinfections in mice was inhibited by ketoconazole therapy. The clinical significance of test results obtained in this study is unknown.

CLINICAL STUDIES

Oropharyngeal Candidiasis:
Two randomized, controlled studies for the treatment of oropharyngeal candidiasis have been conducted (total n = 344). In one trial, clinical response to either 7 or 14 days of itraconazole oral solution, 200 mg/day, was similar to fluconazole tablets and averaged 84% across all arms. Clinical response in this study was defined as cured or improved (only minimal signs and symptoms with no visible lesions). Approximately 5% of subjects were lost to follow-up before any evaluations could be performed. Response to 14 days therapy of itraconazole oral solution was associated with a lower relapse rate than 7 days of itraconazole therapy. In another trial, the clinical response rate (defined as cured or improved) for itraconazole oral solution was similar to clotrimazole troches and averaged approximately 71% across both arms, with approximately 3% of subjects lost to follow-up before any evaluations could be performed. Ninety-two percent of the patients in these studies were HIV seropositive.
In an uncontrolled, open-label study of selected patients clinically unresponsive to fluconazole tablets (n = 74, all patients HIV seropositive), patients were treated with itraconazole oral solution 100 mg b.i.d. (Clinically unresponsive to fluconazole in this study was defined as having received a dose of fluconazole tablets at least 200 mg/day for a minimum of 14 days.) Treatment duration was 14 to 28 days based on response. Approximately 55% of patients had complete resolution of oral lesions. Of patients who responded and then entered a follow-up phase (n = 22), all relapsed within 1 month (median 14 days) when treatment was discontinued. Although baseline endoscopies had not been performed, several patients in this study developed symptoms of esophageal candidiasis while receiving therapy with itraconazole oral solution. Itraconazole oral solution has not been directly compared to other agents in a controlled trial of similar patients.
Esophageal Candidiasis:
A double-blind randomized study (n = 119, 111 of whom were HIV seropositive) compared itraconazole oral solution (100 mg/day) to fluconazole tablets (100 mg/day). The dose of each was increased to 200 mg/day for patients not responding initially. Treatment continued for 2 weeks following resolution of symptoms, for a total duration of treatment of 3 to 8 weeks. Clinical response (a global assessment of cured or improved) was not significantly different between the two study arms, and averaged approximately 86% with 8% lost to follow-up. Six of 53 (11%) itraconazole-treated patients and 12/57 (21%) fluconazole-treated patients were escalated to the 200 mg dose in this trial. Of the subgroup of patients who responded and entered a follow-up phase (n = 88), approximately 23% relapsed across both arms within 4 weeks.

INDICATIONS AND USAGE

Itraconazole oral solution is indicated for the treatment of oropharyngeal and esophageal candidiasis.
(See CLINICAL PHARMACOLOGY: Special Populations, WARNINGS, and ADVERSE REACTIONS: Postmarketing Experience for more information.)

CONTRAINDICATIONS

Congestive Heart Failure:
Itraconazole oral solution should not be administered to patients with evidence of ventricular dysfunction such as congestive heart failure (CHF) or a history of CHF except for the treatment of life-threatening or other serious infections. (See BOXED WARNING, WARNINGS, PRECAUTIONS: Drug Interactions-Calcium Channel Blockers, ADVERSE REACTIONS: Postmarketing Experience, and CLINICAL PHARMACOLOGY: Special Populations.)
Drug Interactions:
Coadministration of a number of CYP3A4 substrates are contraindicated with itraconazole. Some examples of drugs for which plasma concentrations increase are: methadone, disopyramide, dofetilide, dronedarone, quinidine, isavuconazole, ergot alkaloids (such as dihydroergotamine, ergometrine (ergonovine), ergotamine, methylergometrine (methylergonovine)), irinotecan, lurasidone, oral midazolam, pimozide, triazolam, felodipine, nisoldipine, ivabradine, ranolazine, eplerenone, cisapride, naloxegol, lomitapide, lovastatin, simvastatin, avanafil, ticagrelor, finerenone, voclosporin. In addition, coadministration with colchicine, fesoterodine, and solifenacin is contraindicated in subjects with varying degrees of renal or hepatic impairment, and coadministration with eliglustat is contraindicated in subjects that are poor or intermediate metabolizers of CYP2D6 and in subjects taking strong or moderate CYP2D6 inhibitors. (See PRECAUTIONS: Drug Interactions Section for specific examples.) This increase in drug concentrations caused by coadministration with itraconazole may increase or prolong both the pharmacologic effects and/or adverse reactions to these drugs. For example, increased plasma concentrations of some of these drugs can lead to QT prolongation and ventricular tachyarrhythmias including occurrences of torsade de pointes, a potentially fatal arrhythmia. Some specific examples are listed in PRECAUTIONS: Drug Interactions.

Coadministration with venetoclax is contraindicated in patients with CLL/SLL during the dose initiation and ramp-up phase of venetoclax due to the potential for an increased risk of tumor lysis syndrome.

Itraconazole is contraindicated for patients who have shown hypersensitivity to itraconazole. There is limited information regarding cross-hypersensitivity between itraconazole and other azole antifungal agents. Caution should be used when prescribing itraconazole to patients with hypersensitivity to other azoles.

WARNINGS

Hepatic Effects:
Itraconazole has been associated with rare cases of serious hepatotoxicity, including liver failure and death. Some of these cases had neither pre-existing liver disease nor a serious underlying medical condition, and some of these cases developed within the first week of treatment. If clinical signs or symptoms develop that are consistent with liver disease, treatment should be discontinued and liver function testing performed. Continued itraconazole use or reinstitution of treatment with itraconazole is strongly discouraged unless there is a serious or life-threatening situation where the expected benefit exceeds the risk. (See PRECAUTIONS: Information for Patients and ADVERSE REACTIONS.)

Cardiac Dysrhythmias:

Life-threatening cardiac dysrhythmias and/or sudden death have occurred in patients using drugs such as cisapride, pimozide, methadone, or quinidine concomitantly with itraconazole and/or other CYP3A4 inhibitors. Concomitant administration of these drugs with itraconazole oral solution is contraindicated. (See BOXED WARNING, CONTRAINDICATIONS, and PRECAUTIONS: Drug Interactions.)
Cardiac Disease:
Itraconazole oral solution should not be used in patients with evidence of ventricular dysfunction unless the benefit clearly outweighs the risk. For patients with risk factors for congestive heart failure, physicians should carefully review the risks and benefits of itraconazole therapy. These risk factors include cardiac disease such as ischemic and valvular disease; significant pulmonary disease such as chronic obstructive pulmonary disease; and renal failure and other edematous disorders. Such patients should be informed of the signs and symptoms of CHF, should be treated with caution, and should be monitored for signs and symptoms of CHF during treatment. If signs or symptoms of CHF appear during administration of itraconazole oral solution, monitor carefully and consider other treatment alternatives which may include discontinuation of itraconazole oral solution administration.
Itraconazole has been shown to have a negative inotropic effect. When itraconazole was administered intravenously to anesthetized dogs, a dose-related negative inotropic effect was documented. In a healthy volunteer study of itraconazole intravenous infusion, transient, asymptomatic decreases in left ventricular ejection fraction were observed using gated SPECT imaging; these resolved before the next infusion, 12 hours later.
Itraconazole oral solution has been associated with reports of congestive heart failure. In postmarketing experience, heart failure was more frequently reported in patients receiving a total daily dose of 400 mg although there were also cases reported among those receiving lower total daily doses.
Calcium channel blockers can have negative inotropic effects which may be additive to those of itraconazole. In addition, itraconazole can inhibit the metabolism of calcium channel blockers. Therefore, caution should be used when co-administering itraconazole and calcium channel blockers due to an increased risk of CHF. Concomitant administration of itraconazole and felodipine or nisoldipine is contraindicated.
Cases of CHF, peripheral edema, and pulmonary edema have been reported in the postmarketing period among patients being treated for onychomycosis and/or systemic fungal infections. (See CONTRAINDICATIONS, CLINICAL PHARMACOLOGY: Special Populations, PRECAUTIONS: Drug Interactions, and ADVERSE REACTIONS: Postmarketing Experience for more information.)

Pseudoaldosteronism:
Pseudoaldosteronism, manifested by the onset of hypertension or worsening of hypertension, and abnormal laboratory findings (hypokalemia, low serum renin and aldosterone, and elevated 11-deoxycortisol), has been reported with itraconazole use in the postmarketing setting. Monitor blood pressure and potassium levels and manage as necessary. Management of pseudoaldosteronism may include discontinuation of itraconazole, substitution with an appropriate antifungal drug that is not associated with pseudoaldosteronism, or use of aldosterone receptor antagonists.

Interaction Potential:
Itraconazole has a potential for clinically important drug interactions. Coadministration of specific drugs with itraconazole may result in changes in efficacy of itraconazole and/or the coadministered drug, life-threatening effects and/or sudden death. Drugs that are contraindicated, not recommended or recommended for use with caution in combination with itraconazole are listed in PRECAUTIONS: Drug Interactions.
Interchangeability:
Itraconazole oral solution and itraconazole capsules should not be used interchangeably. This is because drug exposure is greater with the oral solution than with the capsules when the same dose of drug is given. Only itraconazole oral solution has been demonstrated effective for oral and/or esophageal candidiasis.
Hydroxypropyl-β-cyclodextrin:
Itraconazole oral solution contains the excipient hydroxypropyl-β-cyclodextrin which produced adenocarcinomas in the large intestine and exocrine pancreatic adenocarcinomas in a rat carcinogenicity study. These findings were not observed in a similar mouse carcinogenicity study. The clinical relevance of these adenocarcinomas is unknown. (See PRECAUTIONS: Carcinogenesis, Mutagenesis, and Impairment of Fertility.)
Treatment of Severely Neutropenic Patients:
Itraconazole oral solution as treatment for oropharyngeal and/or esophageal candidiasis was not investigated in severely neutropenic patients. Due to its pharmacokinetic properties, itraconazole oral solution is not recommended for initiation of treatment in patients at immediate risk of systemic candidiasis.

PRECAUTIONS

Hepatotoxicity:
Rare cases of serious hepatotoxicity have been observed with itraconazole treatment, including some cases within the first week. It is recommended that liver function monitoring be considered in all patients receiving itraconazole. Treatment should be stopped immediately and liver function testing should be conducted in patients who develop signs and symptoms suggestive of liver dysfunction.
Neuropathy:
If neuropathy occurs that may be attributable to itraconazole oral solution, the treatment should be discontinued.
Cystic Fibrosis:
If a patient with cystic fibrosis does not respond to itraconazole oral solution, consideration should be given to switching to alternative therapy (see CLINICAL PHARMACOLOGY: Special Populations).
Hearing Loss:
Transient or permanent hearing loss has been reported in patients receiving treatment with itraconazole. Several of these reports included concurrent administration of quinidine which is contraindicated (see BOXED WARNING: Drug Interactions, CONTRAINDICATIONS: Drug Interactions and PRECAUTIONS: Drug Interactions). The hearing loss usually resolves when treatment is stopped, but can persist in some patients.
Information for Patients:
• Only itraconazole oral solution has been demonstrated effective for oral and/or esophageal candidiasis.
• Itraconazole oral solution contains the excipient hydroxypropyl-β-cyclodextrin which produced adenocarcinomas in the large intestine and exocrine pancreatic adenocarcinomas in a rat carcinogenicity study. These findings were not observed in a similar mouse carcinogenicity study. The clinical relevance of these adenocarcinomas is unknown. (See PRECAUTIONS: Carcinogenesis, Mutagenesis, and Impairment of Fertility.)
• Taking itraconazole oral solution under fasted conditions improves the systemic availability of itraconazole. Instruct patients to take itraconazole oral solution without food, if possible.
• Itraconazole oral solution should not be used interchangeably with itraconazole capsules.
• Instruct patients about the signs and symptoms of congestive heart failure, and if these signs or symptoms occur during itraconazole administration, they should discontinue itraconazole and contact their healthcare provider immediately.
• Instruct patients to stop itraconazole treatment immediately and contact their healthcare provider if any signs and symptoms suggestive of liver dysfunction develop. Such signs and symptoms may include unusual fatigue, anorexia, nausea and/or vomiting, jaundice, dark urine, or pale stools.
• Instruct patients to contact their physician before taking any concomitant medications with itraconazole to ensure there are no potential drug interactions.
• Instruct patients that hearing loss can occur with the use of itraconazole. The hearing loss usually resolves when treatment is stopped, but can persist in some patients. Advise patients to discontinue therapy and inform their physicians if any hearing loss symptoms occur.
• Instruct patients that dizziness or blurred/double vision can sometimes occur with itraconazole. Advise patients that if they experience these events, they should not drive or use machines.
Drug Interactions:
Effect of Itraconazole on Other Drugs
Itraconazole and its major metabolite, hydroxy-itraconazole, are potent CYP3A4 inhibitors. Itraconazole is an inhibitor of the drug transporters P-glycoprotein and breast cancer resistance protein (BCRP). Consequently, itraconazole has the potential to interact with many concomitant drugs resulting in either increased or sometimes decreased concentrations of the concomitant drugs. Increased concentrations may increase the risk of adverse reactions associated with the concomitant drug which can be severe or life-threatening in some cases (e.g., QT prolongation, t orsade de pointes,respiratory depression, hepatic adverse reactions, hypersensitivity reactions, myelosuppression, hypotension, seizures, angioedema, atrial fibrillation, bradycardia, priapism). Reduced concentrations of concomitant drugs may reduce their efficacy. The table below lists examples of drugs that may have their concentrations affected by itraconazole, but it is not a comprehensive list.
Refer to the approved product labeling to become familiar with the interaction pathways, risk potential and specific actions to be taken with regards to each concomitant drug prior to initiating therapy with itraconazole.
Although many of the clinical drug interactions in Table 1 below are based on information with a similar azole antifungal, ketoconazole, these interactions are expected to occur with itraconazole.

Table 1: Drug Interactions with Itraconazole that Affect Concomitant Drug Concentrations
Examples of Concomitant Drugs Within Class |  |  |  | Prevention or Management
Drug Interactions with Itraconazole that Increase Concomitant Drug Concentrations and May Increase Risk of Adverse Reactions Associated with the Concomitant Drug
Alpha Blockers
Alfuzosin Silodosin Tamsulosin |  |  |  | Not recommended during and 2 weeks after itraconazole treatment.
Analgesics
Methadone |  |  |  | Contraindicated during and 2 weeks after itraconazole treatment.
Fentanyl |  |  |  | Not recommended during and 2 weeks after itraconazole treatment.
Alfentanil Buprenorphine (IV and sublingual) Oxycodonea Sufentanil |  |  |  | Monitor for adverse reactions. Concomitant drug dose reduction may be necessary.
Antiarrhythmics
Disopyramide Dofetilide Dronedarone Quinidinea |  |  |  | Contraindicated during and 2 weeks after itraconazole treatment.
Digoxina |  |  |  | Monitor for adverse reactions. Concomitant drug dose reduction may be necessary.
Antibacterials
Bedaquilineb |  |  |  | Concomitant itraconazole not recommended for more than 2 weeks at any time during bedaquiline treatment.
Rifabutin |  |  |  | Not recommended 2 weeks before, during, and 2 weeks after itraconazole treatment. See also Table 2.
Clarithromycin |  |  |  | Monitor for adverse reactions. Concomitant drug dose reduction may be necessary. See also Table 2.
Trimetrexate |  |  |  | Monitor for adverse reactions. Concomitant drug dose reduction may be necessary.
Anticoagulants and Antiplatelets
Ticagrelor |  |  |  | Contraindicated during and 2 weeks after itraconazole treatment.
Apixaban Rivaroxaban Vorapaxar |  |  |  | Not recommended during and 2 weeks after itraconazole treatment.
Cilostazol Dabigatran Warfarin |  |  |  | Monitor for adverse reactions. Concomitant drug dose reduction may be necessary.
Anticonvulsants
Carbamazepine |  |  |  | Not recommended 2 weeks before, during, and 2 weeks after itraconazole treatment. See also Table 2.
Antidiabetic Drugs
Repaglinidea Saxagliptin |  |  |  | Monitor for adverse reactions. Concomitant drug dose reduction may be necessary.
Antihelminthics, Antifungals and Antiprotozoals
Isavuconazonium |  |  |  | Contraindicated during and 2 weeks after itraconazole treatment.
Praziquantel |  |  |  | Monitor for adverse reactions. Concomitant drug dose reduction may be necessary.
Artemether-lumefantrine Quininea |  |  |  | Monitor for adverse reactions.
Antimigraine Drugs
Ergot alkaloids (e.g., dihydroergotamine, ergotamine) |  |  |  | Contraindicated during and 2 weeks after itraconazole treatment.
Eletriptan |  |  |  | Monitor for adverse reactions. Concomitant drug dose reduction may be necessary.
Antineoplastics
Irinotecan |  |  |  | Contraindicated during and 2 weeks after itraconazole treatment.
Venetoclax |  |  |  | Contraindicated during the dose initiation and ramp-up phase in patients with CLL/SLL. Refer to the venetoclax prescribing information for dosing and safety monitoring instructions.
Mobocertiniba |  |  |  | Avoid use during and 2 weeks after itraconazole treatment.
Axitinib Bosutinib Cabazitaxel Cabozantinib Ceritinib Cobimetiniba Crizotinib Dabrafenib Dasatinib Docetaxel | Ibrutinib Lapatinib Nilotinib Olapariba Pazopanib Sunitinib Trabectedin Trastuzumab- emtansine Vinca alkaloids |  |  | Avoid use during and 2 weeks after itraconazole treatment.
Entrectiniba Pemigatiniba Talazopariba |  |  |  | Refer to the entrectinib, pemigatinib and talazoparib prescribing information for dosing instructions if concomitant use cannot be avoided.
Glasdegib |  |  |  | Refer to the glasdegib prescribing information for safety monitoring if concomitant use cannot be avoided.
Bortezomib Brentuximab- vedotin Busulfan Erlotinib Gefitiniba Idelalisib Imatinib Ixabepilone |  |  | Nintedanib Panobinostat Ponatinib Ruxolitinib Sonidegib Tretinoin (oral) Vandetaniba | Monitor for adverse reactions. Concomitant drug dose reduction may be necessary. For idelalisib: see also Table 2.
Antipsychotics, Anxiolytics and Hypnotics
AlprazolamaAripiprazolea Buspironea Cariprazine Diazepama Haloperidola |  | Midazolam (IV)a Quetiapine Ramelteon Risperidonea Suvorexant |  | Monitor for adverse reactions. Concomitant drug dose reduction may be necessary.
Zopiclonea |  |  |  | Monitor for adverse reactions. Concomitant drug dose reduction may be necessary.
Lurasidone Midazolam (oral)a Pimozide Triazolama |  |  |  | Contraindicated during and 2 weeks after itraconazole treatment.
Antivirals
Daclatasvir Indinavira Maraviroc |  |  |  | Monitor for adverse reactions. Concomitant drug dose reduction may be necessary. For indinavir: see also Table 2.
Cobicistat Elvitegravir (ritonavir-boosted) Ombitasvir/Paritaprevir/Ritonavir with or without Dasabuvir Ritonavir Saquinavir (unboosted)a |  |  |  | Monitor for adverse reactions.
Elbasvir/grazoprevir Glecaprevir/pibrentasvir Tenofovir disoproxil fumarate |  |  |  | Not recommended during and 2 weeks after itraconazole treatment. Monitor for adverse reactions. Monitor for adverse reactions.
Beta Blockers
Nadolola |  |  |  | Monitor for adverse reactions. Concomitant drug dose reduction may be necessary.
Calcium Channel Blockers
Felodipinea Nisoldipine |  |  |  | Contraindicated during and 2 weeks after itraconazole treatment.
Diltiazem Other dihydropyridines Verapamil |  |  |  | Monitor for adverse reactions. Concomitant drug dose reduction may be necessary. For diltiazem: see also Table 2.
Cardiovascular Drugs, Miscellaneous
Ivabradine Ranolazine |  |  |  | Contraindicated during and 2 weeks after itraconazole treatment.
Aliskirena Riociguat Sildenafil (for pulmonary hypertension) Tadalafil (for pulmonary hypertension) |  |  |  | Not recommended during and 2 weeks after itraconazole treatment. For sildenafil and tadalafil, see also Urologic Drugs below.
Bosentan Guanfacine |  |  |  | Monitor for adverse reactions. Concomitant drug dose reduction may be necessary.
Contraceptives*
Dienogest Ulipristal |  |  |  | Monitor for adverse reactions.
Diuretics
Eplerenone Finerenone |  |  |  | Contraindicated during and 2 weeks after itraconazole treatment.
Gastrointestinal Drugs
Cisapride Naloxegol |  |  |  | Contraindicated during and 2 weeks after itraconazole treatment.
Aprepitant Loperamidea |  |  |  | Monitor for adverse reactions. Concomitant drug dose reduction may be necessary.
Netupitant |  |  |  | Monitor for adverse reactions.
Immunosuppressants
Voclosporin |  |  |  | Contraindicated during and for 2 weeks after itraconazole treatment.
Everolimus Sirolimus Temsirolimus (IV) |  |  |  | Not recommended during and 2 weeks after itraconazole treatment.
Budesonide (inhalation)a Budesonide (non- Fluticasone (inhalation)a inhalation) Fluticasone (nasal) Ciclesonide Methylprednisolonea (inhalation) Tacrolimus (IV)a Cyclosporine (IV)a Tacrolimus (oral) Cyclosporine (non-IV) Dexamethasonea |  |  |  | Monitor for adverse reactions. Concomitant drug dose reduction may be necessary.
Lipid-Lowering Drugs
Lomitapide Lovastatina Simvastatina |  |  |  | Contraindicated during and 2 weeks after itraconazole treatment.
Atorvastatina |  |  |  | Monitor for drug adverse reactions. Concomitant drug dose reduction may be necessary.
Respiratory Drugs
Salmeterol |  |  |  | Not recommended during and 2 weeks after itraconazole treatment.
SSRIs, Tricyclics and Related Antidepressants
Venlafaxine |  |  |  | Monitor for adverse reactions. Concomitant drug dose reduction may be necessary.
Urologic Drugs
Avanafil |  |  |  | Contraindicated during and 2 weeks after itraconazole treatment.
Fesoterodine |  |  |  | Patients with moderate to severe renal or hepatic impairment: Contraindicated during and 2 weeks after itraconazole treatment. Other patients: Monitor for adverse reactions. Concomitant drug dose reduction may be necessary.
Solifenacin |  |  |  | Patients with severe renal or moderate to severe hepatic impairment: Contraindicated during and 2 weeks after itraconazole treatment. Other patients: Monitor for adverse reactions. Concomitant drug dose reduction may be necessary.
Darifenacin Vardenafil |  |  |  | Not recommended during and 2 weeks after itraconazole treatment.
Dutasteride Oxybutynina Sildenafil (for erectile dysfunction) Tadalafil (for erectile dysfunction and benign prostatic hyperplasia) Tolterodine |  |  |  | Monitor for adverse reactions. Concomitant drug dose reduction may be necessary. For sildenafil and tadalafil, see also Cardiovascular Drugs above.
Miscellaneous Drugs and Other Substances
Colchicine |  |  |  | Patients with renal or hepatic impairment:Contraindicated during and 2 weeks after itraconazole treatment. Other patients: Not recommended during and 2 weeks after itraconazole treatment.
Eliglustat |  |  |  | CYP2D6 EMsc taking a strong or moderate CYP2D6 inhibitor, CYP2D6 IMsc, or CYP2D6 PMsc: Contraindicated during and 2 weeks after itraconazole treatment. CYP2D6 EMscnot taking a strong or moderate CYP2D6 inhibitor : Monitor for adverse reactions. Eliglustat dose reduction may be necessary.
Lumacaftor/Ivacaftor |  |  |  | Not recommended 2 weeks before, during, and 2 weeks after itraconazole treatment.
Alitretinoin (oral) Cabergoline Cannabinoids Cinacalcet Galantamine Ivacaftor |  |  |  | Monitor for adverse reactions. Concomitant drug dose reduction may be necessary.
Valbenazine |  |  |  | Concomitant drug dose reduction is necessary. Refer to the valbenazine prescribing information for dosing instructions.
Vasopressin Receptor Antagonists
Conivaptan Tolvaptan |  |  |  | Not recommended during and 2 weeks after itraconazole treatment.
Drug Interactions with Itraconazole that Decrease Concomitant Drug Concentrations and May Reduce Efficacy of the Concomitant Drug
Antineoplastics
Regorafenib |  |  |  | Not recommended during and 2 weeks after itraconazole treatment.
Gastrointestinal Drugs
Saccharomyces boulardii |  |  |  | Not recommended during and 2 weeks after itraconazole treatment.
Nonsteroidal Anti-Inflammatory Drugs
Meloxicama |  |  |  | Concomitant drug dose increase may be necessary.

*CYP3A4 inhibitors (including itraconazole) may increase systemic contraceptive hormone concentrations.

aBased on clinical drug interaction information with itraconazole.
bBased on 400 mg bedaquiline once daily for 2 weeks.
cEMs: extensive metabolizers; IMs: intermediate metabolizers, PMs: poor metabolizers
Effect of Other Drugs on Itraconazole
Itraconazole is mainly metabolized through CYP3A4. Other substances that either share this metabolic pathway or modify CYP3A4 activity may influence the pharmacokinetics of itraconazole. Some concomitant drugs have the potential to interact with itraconazole resulting in either increased or sometimes decreased concentrations of itraconazole. Increased concentrations may increase the risk of adverse reactions associated with itraconazole. Decreased concentrations may reduce itraconazole efficacy.
The table below lists examples of drugs that may affect itraconazole concentrations, but it is not a comprehensive list. Refer to the approved product labeling to become familiar with the interaction pathways, risk potential and specific actions to be taken with regards to each concomitant drug prior to initiating therapy with itraconazole.
Although many of the clinical drug interactions in Table 2 below are based on information with a similar azole antifungal, ketoconazole, these interactions are expected to occur with itraconazole.

Table 2: Drug Interactions with Other Drugs that Affect Itraconazole Concentrations
Examples of Concomitant Drugs Within Class | Prevention or Management
Drug Interactions with Other Drugs that Increase Itraconazole Concentrations and May Increase Riskof Adverse Reactions Associated with Itraconazole
Antibacterials
Ciprofloxacina Erythromycina Clarithromycina | Monitor for adverse reactions. Itraconazole dose reduction may be necessary.
Antineoplastics
Idelalisib | Monitor for adverse reactions. Itraconazole dose reduction may be necessary. See also Table 1.
Antivirals
Cobicistat Darunavir (ritonavir-boosted) Elvitegravir (ritonavir-boosted) Fosamprenavir (ritonavir-boosted) Indinavira Ombitasvir/ Paritaprevir/ Ritonavir with or without Dasabuvir Ritonavir Saquinavir | Monitor for adverse reactions. Itraconazole dose reduction may be necessary. For Boceprevir, cobicistat, elvitegravir, indinavir, ombitasvir/ paritaprevir/ ritonavir with or without dasabuvir, ritonavir and saquinavir, see also Table 1.
Calcium Channel Blockers
Diltiazem | Monitor for adverse reactions. Itraconazole dose reduction may be necessary. See also the table above.
Drug Interactions with Other Drugs that Decrease Itraconazole Concentrations and May Reduce Efficacy of Itraconazole
Antibacterials
Isoniazid Rifampicina | Not recommended 2 weeks before and during itraconazole treatment.
Rifabutina | Not recommended 2 weeks before, during, and 2 weeks after itraconazole treatment. See also Table 1.
Anticonvulsants
Phenobarbital Phenytoina | Not recommended 2 weeks before and during itraconazole treatment.
Carbamazepine | Not recommended 2 weeks before, during, and 2 weeks after itraconazole treatment. See also Table 1.
Antivirals
Efavirenza Nevirapinea | Not recommended 2 weeks before and during itraconazole treatment.
Miscellaneous Drugs and Other Substances
Lumacaftor/Ivacaftor | Not recommended 2 weeks before, during, and 2 weeks after itraconazole treatment.

aBased on clinical drug interaction information with itraconazole.

Pediatric Population
Interaction studies have only been performed in adults.
Carcinogenesis, Mutagenesis, and Impairment of Fertility:
Itraconazole
Itraconazole showed no evidence of carcinogenicity potential in mice treated orally for 23 months at dosage levels up to 80 mg/kg/day (approximately 1 time the maximum recommended human dose [MRHD] of 400 mg/day based on body surface area comparisons). Male rats treated with 25 mg/kg/day (0.6 times the MRHD based on body surface area comparisons) had a slightly increased incidence of soft tissue sarcoma. These sarcomas may have been a consequence of hypercholesterolemia, which is a response of rats, but not dogs or humans, to chronic itraconazole administration. Female rats treated with 50 mg/kg/day (1.2 times the MRHD based on body surface area comparisons) had an increased incidence of squamous cell carcinoma of the lung (2/50) as compared to the untreated group. Although the occurrence of squamous cell carcinoma in the lung is extremely uncommon in untreated rats, the increase in this study was not statistically significant.
Itraconazole produced no mutagenic effects when assayed in DNA repair test (unscheduled DNA synthesis) in primary rat hepatocytes, in Ames tests with Salmonella typhimurium(6 strains) and Escherichia coli,in the mouse lymphoma gene mutation tests, in a sex-linked recessive lethal mutation (Drosophila melanogaster) test, in chromosome aberration tests in human lymphocytes, in a cell transformation test with C3H/10T½ C18 mouse embryo fibroblasts cells, in a dominant lethal mutation test in male and female mice, and in micronucleus tests in mice and rats.
Itraconazole did not affect the fertility of male or female rats treated orally with dosage levels of up to 40 mg/kg/day (1 time the MRHD based on body surface area comparisons), even though parental toxicity was present at this dosage level. More severe signs of parental toxicity, including death, were present in the next higher dosage level, 160 mg/kg/day (4 times the MRHD based on body surface area comparisons).
Hydroxypropyl-β-cyclodextrin (HP-β-CD)
Hydroxypropyl-β-cyclodextrin (HP-β-CD) is the solubilizing excipient used in itraconazole oral solution.
Hydroxypropyl-β-cyclodextrin (HP-β-CD) was found to produce neoplasms in the large intestine at 5,000 mg/kg/day in rat carcinogenicity study. This dose was about 3 times amount contained in the recommended clinical dose of itraconazole oral solution (16 g) based on body surface area comparisons. The clinical relevance of this finding is unknown. The slightly higher incidence of adenocarcinomas in the large intestines was linked to the hypertrophic/hyperplastic and inflammatory changes in the colonic mucosa brought about by HP-β-CD-induced increased osmotic forces.
In addition, HP-β-CD was found to produce pancreatic exocrine hyperplasia and neoplasia when administered orally to rats at doses of 500, 2,000 or 5,000 mg/kg/day for 25 months. Adenocarcinomas of the exocrine pancreas produced in the treated animals were not seen in the untreated group and are not reported in the historical controls. The maximum recommended clinical dose of itraconazole oral solution contains approximately 3.3 times the amount of HP-β-CD as was in the 500 mg/kg/day dose, based on body surface area comparisons. This finding was not observed in the mouse carcinogenicity study at doses of 500, 2,000 or 5,000 mg/kg/day for 22 to 23 months. This finding was also not observed in a 12-month toxicity study in dogs or in a 2-year toxicity study in female cynomolgus monkeys.
Since the development of the pancreatic tumors may be related to a mitogenic action of cholecystokinin and since there is no evidence that cholecystokinin has a mitogenic action in man, the clinical relevance of these findings is unknown.
HP-β-CD has no antifertile effect, and is not mutagenic.
Pregnancy: Teratogenic Effects:
Itraconazole was found to cause a dose-related increase in maternal toxicity, embryotoxicity, and teratogenicity in rats at dosage levels of approximately 40 to 160 mg/kg/day (1 to 4 times the MRHD based on body surface area comparisons), and in mice at dosage levels of approximately 80 mg/kg/day (1 time the MRHD based on body surface area comparisons). Itraconazole has been shown to cross the placenta in a rat model. In rats, the teratogenicity consisted of major skeletal defects; in mice, it consisted of encephaloceles and/or macroglossia.
Itraconazole oral solution contains the excipient hydroxypropyl-β-cyclodextrin (HP-β-CD). HP-β-CD has no direct embryotoxic and no teratogenic effect.
There are no studies in pregnant women. Itraconazole should be used in pregnancy only if the benefit outweighs the potential risk. Highly effective contraception should be continued throughout itraconazole therapy and for 2 months following the end of treatment.
During postmarketing experience, cases of congenital abnormalities have been reported. (See ADVERSE REACTIONS: Postmarketing Experience.)
Nursing Mothers:
Itraconazole is excreted in human milk; therefore, the expected benefits of itraconazole therapy for the mother should be weighed against the potential risk from exposure of itraconazole to the infant. The U.S. Public Health Service Centers for Disease Control and Prevention advises HIV-infected women not to breast-feed to avoid potential transmission of HIV to uninfected infants.
Pediatric Use:
The efficacy and safety of itraconazole have not been established in pediatric patients.
The long-term effects of itraconazole on bone growth in children are unknown. In three toxicology studies using rats, itraconazole induced bone defects at dosage levels as low as 20 mg/kg/day (0.5 times the MRHD of 400 mg based on body surface area comparisons). The induced defects included reduced bone plate activity, thinning of the zona compacta of the large bones, and increased bone fragility. At a dosage level of 80 mg/kg/day (2 times the MRHD based on body surface area comparisons) over 1 year or 160 mg/kg/day (4 times the MRHD based on body surface area comparisons) for 6 months, itraconazole induced small tooth pulp with hypocellular appearance in some rats.
Geriatric Use:
Clinical studies of itraconazole oral solution did not include sufficient numbers of subjects aged 65 years and over to determine whether they respond differently from younger subjects. It is advised to use itraconazole oral solution in these patients only if it is determined that the potential benefit outweighs the potential risks. In general, it is recommended that the dose selection for an elderly patient should be taken into consideration, reflecting the greater frequency of decreased hepatic, renal, or cardiac function, and of concomitant disease or other drug therapy.
Transient or permanent hearing loss has been reported in elderly patients receiving treatment with itraconazole. Several of these reports included concurrent administration of quinidine which is contraindicated (see BOXED WARNING: Drug Interactions, CONTRAINDICATIONS: Drug Interactions and PRECAUTIONS: Drug Interactions).
Renal Impairment:
Limited data are available on the use of oral itraconazole in patients with renal impairment. The exposure of itraconazole may be lower in some patients with renal impairment. Caution should be exercised when itraconazole is administered in this patient population and dose adjustment may be needed. (See CLINICAL PHARMACOLOGY: Special Populations and DOSAGE AND ADMINISTRATION.)
Hepatic Impairment:
Limited data are available on the use of oral itraconazole in patients with hepatic impairment. Caution should be exercised when this drug is administered in this patient population. It is recommended that patients with impaired hepatic function be carefully monitored when taking itraconazole. It is recommended that the prolonged elimination half-life of itraconazole observed in the single oral dose clinical trial with itraconazole capsules in cirrhotic patients be considered when deciding to initiate therapy with other medications metabolized by CYP3A4.
In patients with elevated or abnormal liver enzymes or active liver disease, or who have experienced liver toxicity with other drugs, treatment with itraconazole is strongly discouraged unless there is a serious or life-threatening situation where the expected benefit exceeds the risk. It is recommended that liver function monitoring be done in patients with pre-existing hepatic function abnormalities or those who have experienced liver toxicity with other medications. (See CLINICAL PHARMACOLOGY: Special Populations and DOSAGE AND ADMINISTRATION.)

ADVERSE REACTIONS

Because clinical trials are conducted under widely varying conditions, adverse reaction rates observed in the clinical trials of a drug cannot be directly compared to rates in the clinical trials of another drug and may not reflect the rates observed in clinical practice.
Itraconazole has been associated with rare cases of serious hepatotoxicity, including liver failure and death. Some of these cases had neither pre-existing liver disease nor a serious underlying medical condition. If clinical signs or symptoms develop that are consistent with liver disease, treatment should be discontinued and liver function testing performed. The risks and benefits of itraconazole use should be reassessed. (See WARNINGS: Hepatic Effects and PRECAUTIONS: Hepatotoxicity and Information for Patients.)
Adverse Events Reported in Oropharyngeal or Esophageal Candidiasis Trials
U.S. adverse experience data are derived from 350 immunocompromised patients (332 HIV seropositive/AIDS) treated for oropharyngeal or esophageal candidiasis. Table 3 below lists adverse events reported by at least 2% of patients treated with itraconazole oral solution in U.S. clinical trials. Data on patients receiving comparator agents in these trials are included for comparison.

Table 3: Summary of Adverse Events Reported by ≥2% of Itraconazole Treated Patients in U.S. Clinical Trials (Total)

Body System/ Adverse Event | Itraconazole
Body System/ Adverse Event | Total (n = 350*) % | All controlled studies (n = 272) % | Fluconazole (n = 125†) % | Clotrimazole (n = 81‡) %
Gastrointestinal disorders
Nausea Diarrhea Vomiting Abdominal pain Constipation | 11 11 7 6 2 | 10 10 6 4 2 | 11 10 8 7 1 | 5 4 1 7 0
Body as a whole
Fever Chest pain Pain Fatigue | 7 3 2 2 | 6 3 2 1 | 8 2 4 2 | 5 0 0 0
Respiratory disorders
Coughing Dyspnea Pneumonia Sinusitis Sputum increased | 4 2 2 2 2 | 4 3 2 2 3 | 10 5 0 4 3 | 0 1 0 0 1
Skin and appendages disorders
Rash Increased sweating Skin disorder unspecified | 4 3 2 | 5 4 2 | 4 6 2 | 6 1 1
Central/peripheral nervous system
Headache Dizziness | 4 2 | 4 2 | 6 4 | 6 1
Resistance mechanism disorders
Pneumocystis carinii infection | 2 | 2 | 2 | 0
Psychiatric disorders
Depression | 2 | 1 | 0 | 1

*Of the 350 patients, 209 were treated for oropharyngeal candidiasis in controlled studies, 63 were treated for esophageal candidiasis in controlled studies and 78 were treated for oropharyngeal candidiasis in an open study.

† Of the 125 patients, 62 were treated for oropharyngeal candidiasis and 63 were treated for esophageal candidiasis.

‡All 81 patients were treated for oropharyngeal candidiasis.

Adverse events reported by less than 2% of patients in U.S. clinical trials with itraconazole included: adrenal insufficiency, asthenia, back pain, dehydration, dyspepsia, dysphagia, flatulence, gynecomastia, hematuria, hemorrhoids, hot flushes, implantation complication, infection unspecified, injury, insomnia, male breast pain, myalgia, pharyngitis, pruritus, rhinitis, rigors, stomatitis ulcerative, taste perversion, tinnitus, upper respiratory tract infection, vision abnormal, and weight decrease. Edema, hypokalemia and menstrual disorders have been reported in clinical trials with itraconazole capsules.

Adverse Events Reported from Other Clinical Trials

A comparative clinical trial in patients who received intravenous itraconazole followed by itraconazole oral solution or received Amphotericin B reported the following adverse events in the itraconazole intravenous/itraconazole oral solution treatment arm which are not listed above in the subsection “Adverse Events Reported in Oropharyngeal or Esophageal Candidiasis Trials” or listed below as postmarketing reports of adverse drug reactions: serum creatinine increased, blood urea nitrogen increased, renal function abnormal, hypocalcemia, hypomagnesemia, hypophosphatemia, hypotension, tachycardia and pulmonary infiltration.
In addition, the following adverse drug reactions were reported in patients who participated in itraconazole oral solution clinical trials:

Cardiac Disorders:cardiac failure;

General Disorders and Administration Site Conditions:edema;
Hepatobiliary Disorders:hepatic failure, hyperbilirubinemia;
Metabolism and Nutrition Disorders:hypokalemia;
Reproductive System and Breast Disorders:menstrual disorder
The following is a list of additional adverse drug reactions associated with itraconazole that have been reported in clinical trials of itraconazole capsules and itraconazole IV excluding the adverse reaction term “Injection site inflammation” which is specific to the injection route of administration:
Cardiac Disorders:left ventricular failure;
Gastrointestinal Disorders:gastrointestinal disorder;
General Disorders and Administration Site Conditions:face edema;
Hepatobiliary Disorders:jaundice, hepatic function abnormal;
Investigations:alanine aminotransferase increased, aspartate aminotransferase increased, blood alkaline phosphatase increased, blood lactate dehydrogenase increased, gamma-glutamyltransferase increased, urine analysis abnormal;
Metabolism and Nutrition Disorders:hyperglycemia, hyperkalemia;
Nervous System Disorders:somnolence;
Psychiatric Disorders:confusional state;
Renal and Urinary Disorders:renal impairment;
Respiratory, Thoracic and Mediastinal Disorders:dysphonia;
Skin and Subcutaneous Tissue Disorders:rash erythematous;
Vascular Disorders:hypertension
In addition, the following adverse drug reaction was reported in children only who participated in itraconazole oral solution clinical trials: mucosal inflammation.

Postmarketing Experience

Adverse drug reactions that have been first identified during postmarketing experience with itraconazole (all formulations) are listed in Table 4 below. Because these reactions are reported voluntarily from a population of uncertain size, reliably estimating their frequency or establishing a causal relationship to drug exposure is not always possible.

Table 4: Postmarketing Reports of Adverse Drug Reactions

Blood and Lymphatic System Disorders: | Leukopenia, neutropenia, thrombocytopenia
Immune System Disorders: | Anaphylaxis; anaphylactic, anaphylactoid and allergic reactions; serum sickness; angioneurotic edema
Endocrine Disorders: | Pseudoaldosteronism
Metabolism and Nutrition Disorders: | Hypertriglyceridemia
Nervous System Disorders: | Peripheral neuropathy, paresthesia, hypoesthesia, tremor
Eye Disorders: | Visual disturbances, including vision blurred and diplopia
Ear and Labyrinth Disorders: | Transient or permanent hearing loss
Cardiac Disorders: | Congestive heart failure, bradycardia
Respiratory, Thoracic and Mediastinal Disorders: | Pulmonary edema
Gastrointestinal Disorders: | Pancreatitis
Hepatobiliary Disorders: | Serious hepatotoxicity (including some cases of fatal acute liver failure), hepatitis, reversible increases in hepatic enzymes
Skin and Subcutaneous Tissue Disorders: | Toxic epidermal necrolysis, Stevens-Johnson syndrome, acute generalized exanthematous pustulosis, erythema multiforme, exfoliative dermatitis, leukocytoclastic vasculitis, alopecia, photosensitivity, urticaria
Musculoskeletal and Connective Tissue Disorders: | Arthralgia
Renal and Urinary Disorders: | Urinary incontinence, pollakiuria
Reproductive System and Breast Disorders: | Erectile dysfunction
General Disorders and Administration Site Conditions: | Peripheral edema
Investigations: | Blood creatine phosphokinase increased

There is limited information on the use of itraconazole during pregnancy. Cases of congenital abnormalities including skeletal, genitourinary tract, cardiovascular and ophthalmic malformations as well as chromosomal and multiple malformations have been reported during postmarketing experience. A causal relationship with itraconazole has not been established. (See CLINICAL PHARMACOLOGY: Special Populations, CONTRAINDICATIONS, WARNINGS, and PRECAUTIONS: Drug Interactions for more information.)

OVERDOSAGE

Itraconazole is not removed by dialysis. In the event of accidental overdosage, supportive measures should be employed. Contact a certified poison control center for the most up to date information on the management of itraconazole oral solution overdosage (1-800-222-1222 or www.poison.org). In general, adverse events reported with overdose have been consistent with adverse drug reactions already listed in this package insert for itraconazole. (See ADVERSE REACTIONS.)

DOSAGE AND ADMINISTRATION

Treatment of Oropharyngeal and Esophageal Candidiasis:
The solution should be vigorously swished in the mouth (10 mL at a time) for several seconds and swallowed.
The recommended dosage of itraconazole oral solution for oropharyngeal candidiasis is 200 mg (20 mL) daily for 1 to 2 weeks. Clinical signs and symptoms of oropharyngeal candidiasis generally resolve within several days.
For patients with oropharyngeal candidiasis unresponsive/refractory to treatment with fluconazole tablets, the recommended dose is 100 mg (10 mL) b.i.d. For patients responding to therapy, clinical response will be seen in 2 to 4 weeks. Patients may be expected to relapse shortly after discontinuing therapy. Limited data on the safety of long-term use (>6 months) of itraconazole oral solution are available at this time.
The recommended dosage of itraconazole oral solution for esophageal candidiasis is 100 mg (10 mL) daily for a minimum treatment of three weeks. Treatment should continue for 2 weeks following resolution of symptoms. Doses up to 200 mg (20 mL) per day may be used based on medical judgment of the patient’s response to therapy.
Itraconazole oral solution and itraconazole capsules should not be used interchangeably. Patients should be instructed to take itraconazole oral solution without food, if possible. Only itraconazole oral solution has been demonstrated effective for oral and/or esophageal candidiasis.
Use in Patients with Renal Impairment:
Limited data are available on the use of oral itraconazole in patients with renal impairment. Caution should be exercised when this drug is administered in this patient population. (See CLINICAL PHARMACOLOGY: Special Populations and PRECAUTIONS.)
Use in Patients with Hepatic Impairment:
Limited data are available on the use of oral itraconazole in patients with hepatic impairment. Caution should be exercised when this drug is administered in this patient population. (See CLINICAL PHARMACOLOGY: Special Populations, WARNINGS, and PRECAUTIONS.)

HOW SUPPLIED

Itraconazole Oral Solution is available in 150 mL amber glass bottles (NDC 31722-006-31) containing 10 mg of itraconazole per mL.
Store at 20° to 25°C (68° to 77°F) [see USP Controlled Room Temperature]. Do not freeze.

Manufactured for:
Camber Pharmaceuticals, Inc.
Piscataway, NJ 08854.

By: Annora Pharma Pvt. Ltd.
Sangareddy - 502313, Telangana, India.

Revised: 01/2025

PACKAGE LABEL.PRINCIPAL DISPLAY PANEL

Itraconazole Oral Solution 10 mg/mL carton label

Itraconazole Oral Solution 10 mg/mL container label